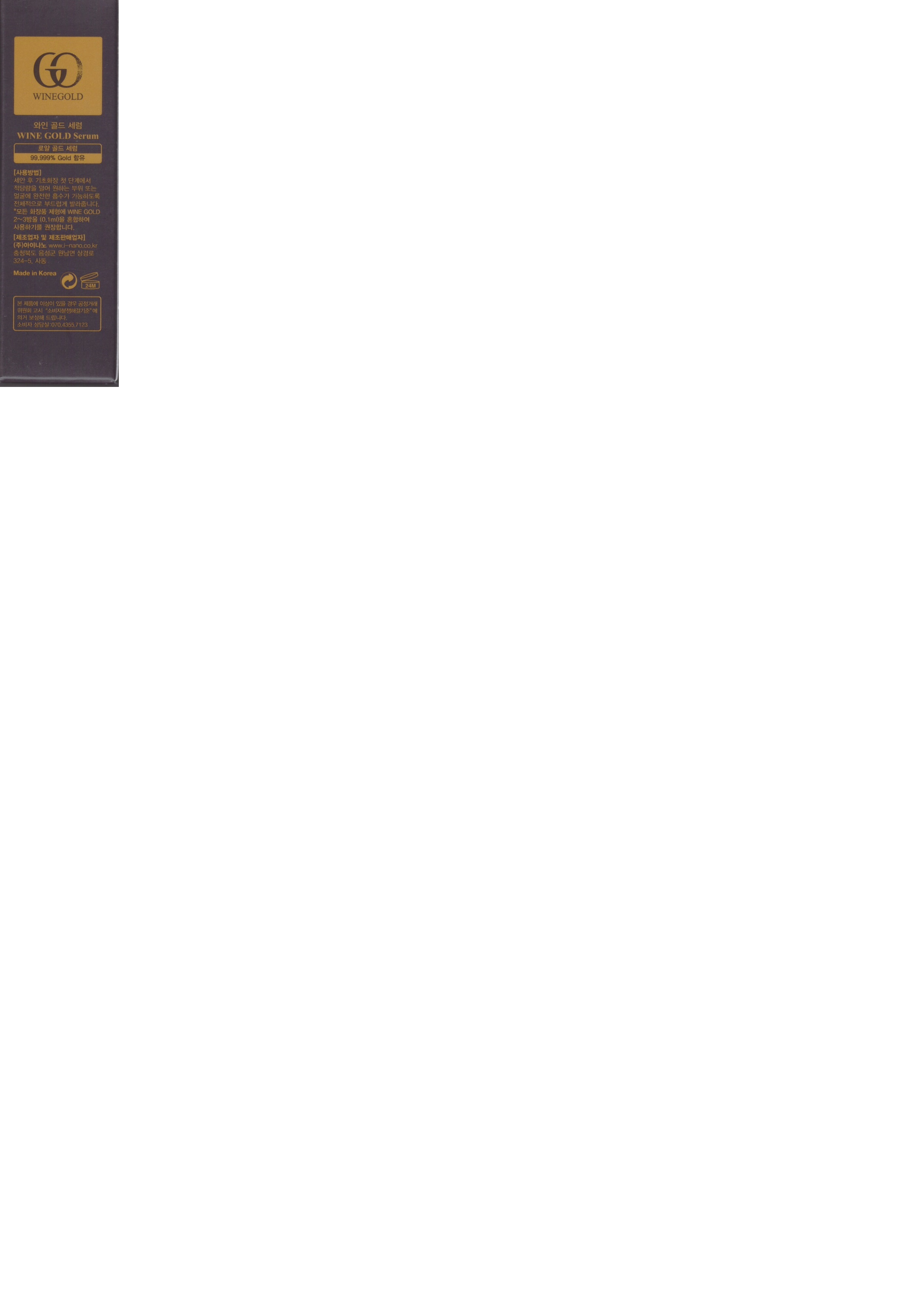 DRUG LABEL: Wine Gold Serum
NDC: 72160-0002 | Form: LIQUID
Manufacturer: iNANO Co., Ltd.
Category: otc | Type: HUMAN OTC DRUG LABEL
Date: 20180311

ACTIVE INGREDIENTS: DIMETHICONE 99.97 g/100 mL
INACTIVE INGREDIENTS: GOLD

ACTIVE INGREDIENT

dimethicone

INACTIVE INGREDIENT

gold

PURPOSE

scalp care

WARNINGS

1. If the following symptoms occur after product use, stop using the product immediately and consult a dermatologist (continuous use can exacerbate the symptoms).
1) Occurrence of red spots, swelling, itchiness, and other skin irritation
2) If the symptoms above occur after the application area is exposed to direct sunlight

2. Do not use on open wounds, eczema, and other skin irritations
3. Precaution for Storage and Handling
- Keep out of reach of infants and children
- Do not to store in a place with high/low temperature and exposed to direct sunlight

Keep out of reach of children.

INDICATIONS AND USAGE

[for use with mask sheet]

1. after washing, remove moisture entirely to arrange skin texture

2. apply the wine gold serum (step 1) onto the face equaly and rub the serum softly like massae to absorb perfectly

3. unfolding the mask (step 2), position the mask on the fact according to position of eyes and mouth

4. remove the mask sheet after 15~30 minutes, after that softly pat any remaining essence into skin like massage

[for scalp care]

apply proper amount to the scalp

DOSAGE AND ADMINISTRATION

for external use only